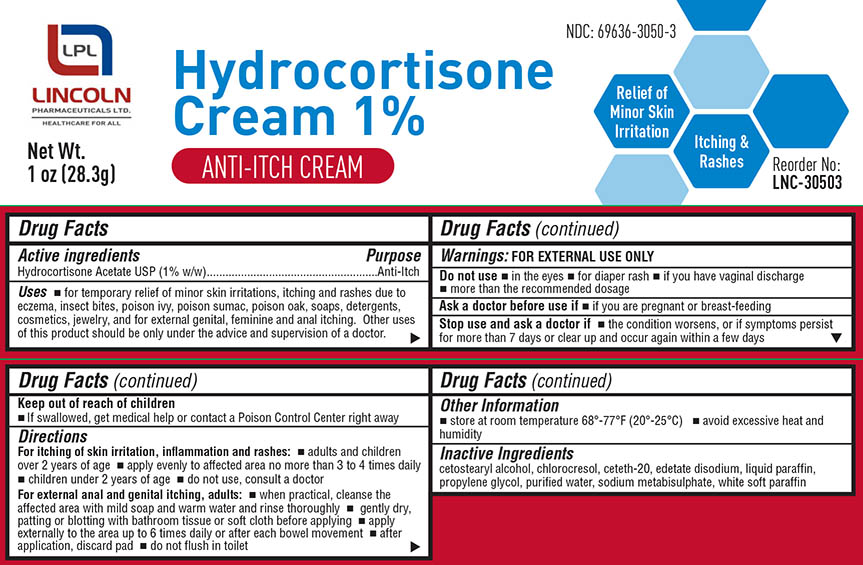 DRUG LABEL: Lincoln
NDC: 69636-3050 | Form: CREAM
Manufacturer: Lincoln Pharmaceuticals Ltd.
Category: otc | Type: HUMAN OTC DRUG LABEL
Date: 20160405

ACTIVE INGREDIENTS: HYDROCORTISONE ACETATE 0.01 g/1 g
INACTIVE INGREDIENTS: CHLOROCRESOL; CETETH-20; EDETATE DISODIUM; MINERAL OIL; PROPYLENE GLYCOL 1,2-DISTEARATE; WATER; SODIUM METABISULFITE; PETROLATUM; CETOSTEARYL ALCOHOL

Drug Facts

Hydrocortisone Acetate USP (1 % W/W)

Drug Facts

Anti-Itch

Drug Facts

for external use only

USES

- For temporary relief of minor skin irritations, itching and rashes due to eczema, insect bites, poison ivy position sumac, poison oak, soaps, detergents, cosmetics, jewelry, and for external genital, feminine and anal itching. Other uses of this product should be only under the advice and supervision of a doctor

Drug Facts

- in the eyes
- for diaper rash
- if you have a vaginal discharge
- more than the recommended dosage

Drug Facts

If you are pregnant or breast- feeding

Drug Facts

- the condition worsens, or if symptoms persist for more than 7 days or clear up and occur again within a few days

Drug Facts

- If swallowed, get medical help or contact a Poison Control Center right away

Drug facts

For Itching of skin irritation, inflammation and rashes:

- adults and children over 2 years of age
- apply evenly to affected area no more than 3 to 4 times daily

Children under 2 years of age

- Do not use, consult a doctor

For External anal and genital itching, adults:

- when practical cleanse the affected area with mild soap and warm water and rinse thoroughly
- gently dry, patting or blotting with bathroom tissue or soft cloth before applying
- apply externally to the area upto 6 times daily or after each bowel movement
- after application, discard pad
- do not flush in toilet

Drug Facts

Cetostearyl alcohol, chlorocresol, ceteth-20, edetate disodium, liquid paraffin, propylene glycol, purified water, sodium metabisulphite, white soft paraffin

Drug Facts:

- store at room temperature 68-77 F (20°-25°C)
- avoid excessive heat and humidity